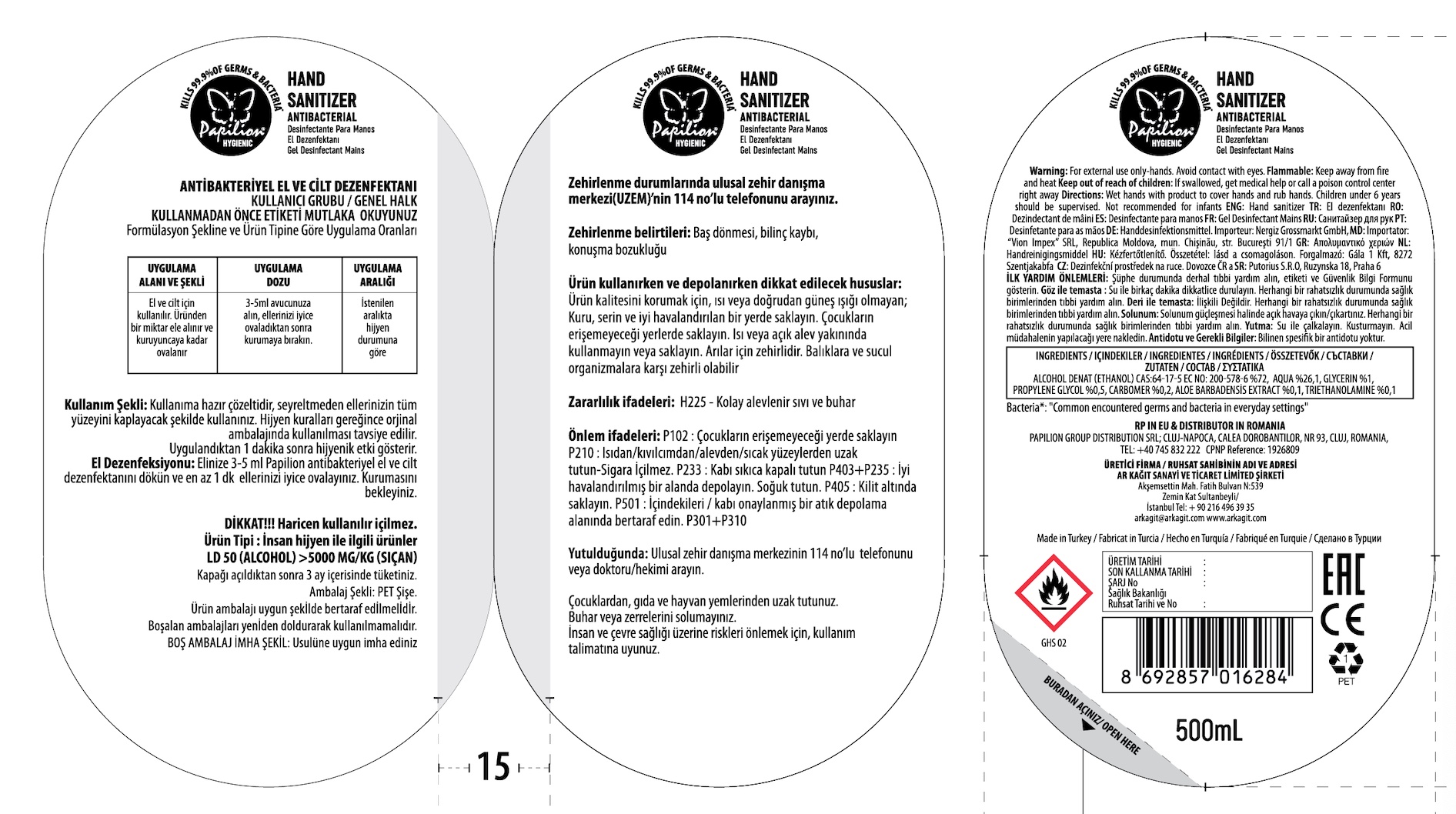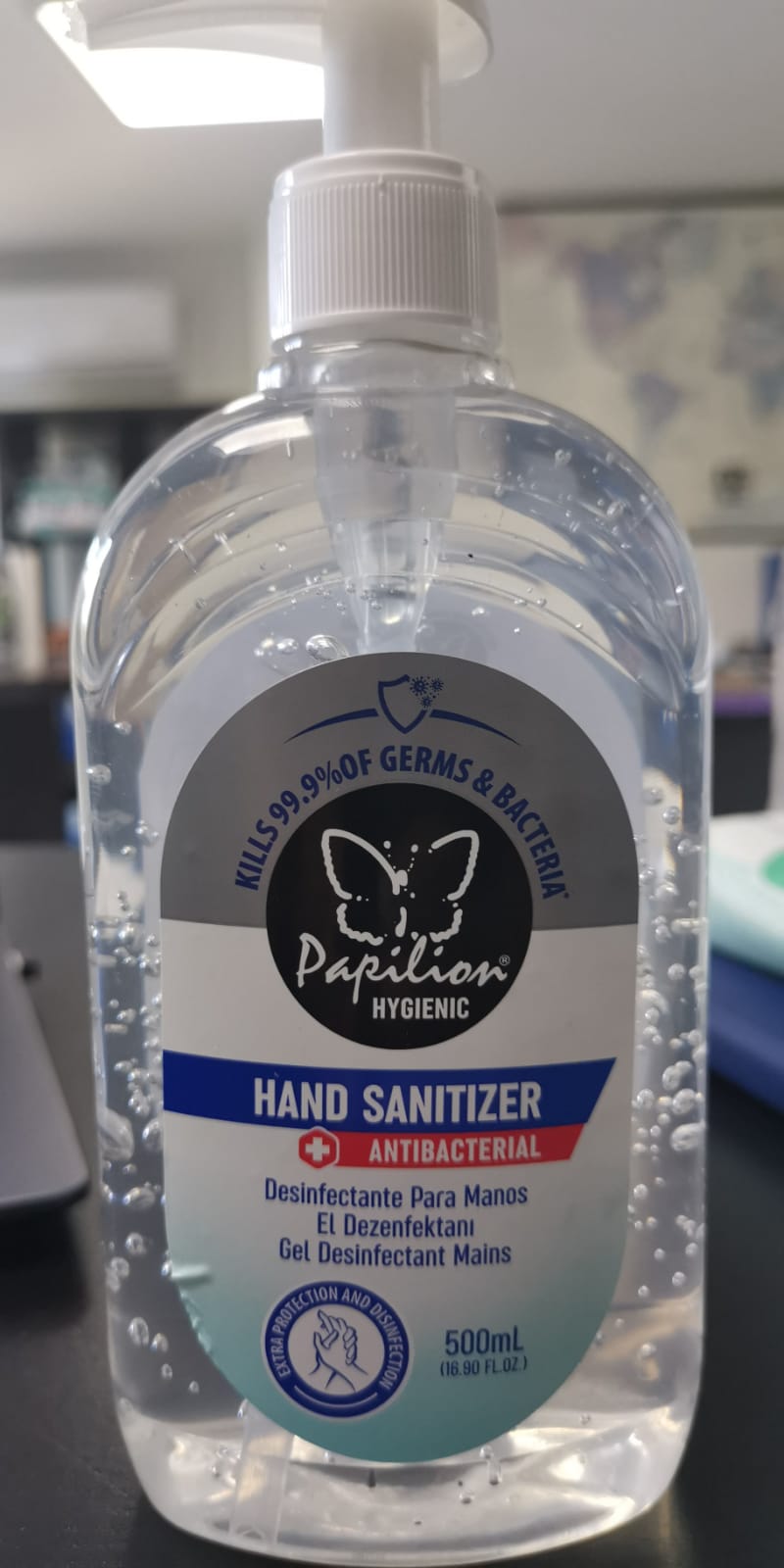 DRUG LABEL: PAPILION HYGIENIC ANTIBACTERIAL HAND SANITIZER
NDC: 79262-110 | Form: GEL
Manufacturer: AR KAGIT SAN. ve TIC. LTD. STI.
Category: otc | Type: HUMAN OTC DRUG LABEL
Date: 20210228

ACTIVE INGREDIENTS: ALCOHOL 75 mL/100 mL
INACTIVE INGREDIENTS: GLYCERIN 0.5 mL/100 mL; CARBOMER 940 0.33 mL/100 mL; WATER; ALOE VERA LEAF 0.1 mL/100 mL; TROLAMINE 0.2 mL/100 mL; PROPYLENE GLYCOL 0.25 mL/100 mL

This is a hand sanitizer manufactured according to the Temporary Policy for Preparation of Certain Alcohol-Based Hand Sanitizer Products During the Public Health Emergency (CoViD-19); Guidance for Industry.

The hand sanitizer is manufactured using only the following United States Pharmacopoeia (USP) grade ingredients in the preparation of the product (percentage in final product formulation) consistent with) recommendations:

1. Alcohol (ethanol) (USP or Food Chemical Codex (FCC) grade) (75%, volume/volume (v/v)) in an aqueous solution denatured according to Alcohol and Tobacco Tax and Trade Bureau regulations in 27 CFR part 20.
2. Glycerol (0.5% v/v).
3. Aloe Vera Leaf (0.1% v/v).
4. Carbomer 940 (0.33% v/v).
5. Triethanolamin (0.2% v/v).
6. Sterile distilled water

The firm does not add other active or inactive ingredients. Different or additional ingredients may impact the quality and potency of the product.

Active Ingredient(s)

Alcohol 75% v/v. Purpose: Antiseptic

Purpose

Antiseptic, Papilion Hygienic Antibacterial Hand Sanitizer

Uses

Uses hand sanitizer to help reduce bacteria on the skin that could cause disease

Warnings

For external use only. Flammable. Keep away from fire or flame.

When using this product do not get into eyes. If contact occurs, rinse thoroughly with water.

Stop use and ask a doctor if irritation or rash appears and lasts.

Stop use and ask a doctor if irritation or redness devolops and lasts.

Keep out of reach of children if swallowed, get medical help or contact a Poison Control Center right away.

Directions

- Put enough product in your palm to cover hands and rub hands together until dry.
- Children under 6 years should be supervised when using this product.

Other information

- Store below 106 F (41 C).
- May discolor certain fabrics or surfaces.

Inactive ingredients

Water (Aqua), Glycerin, Propylene Glycol, Carbomer, Aloe Barbadensis Leaf Juice, Triethanolamine.

Package Label - Principal Display Panel

500 mL NDC: 79262-110-02